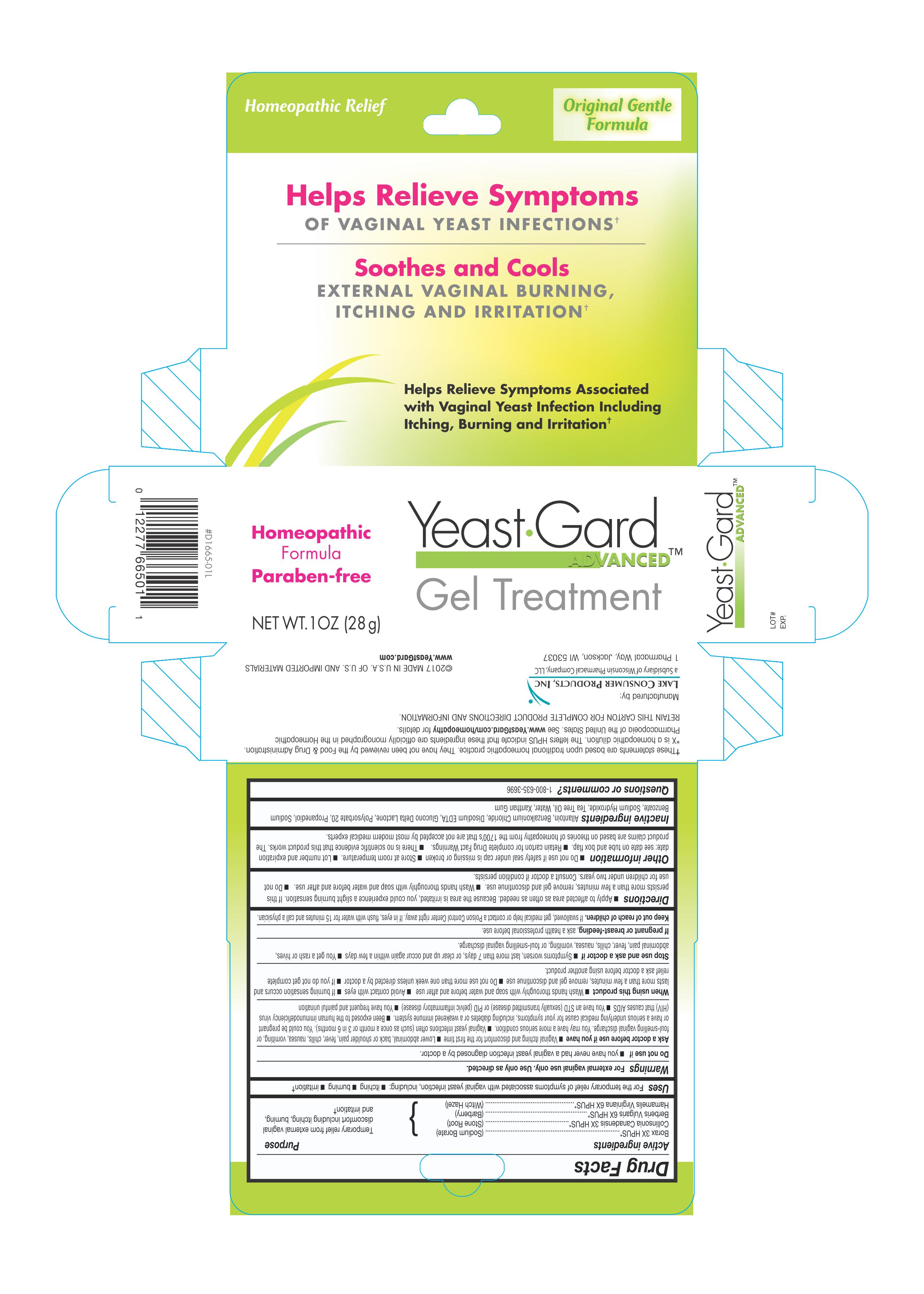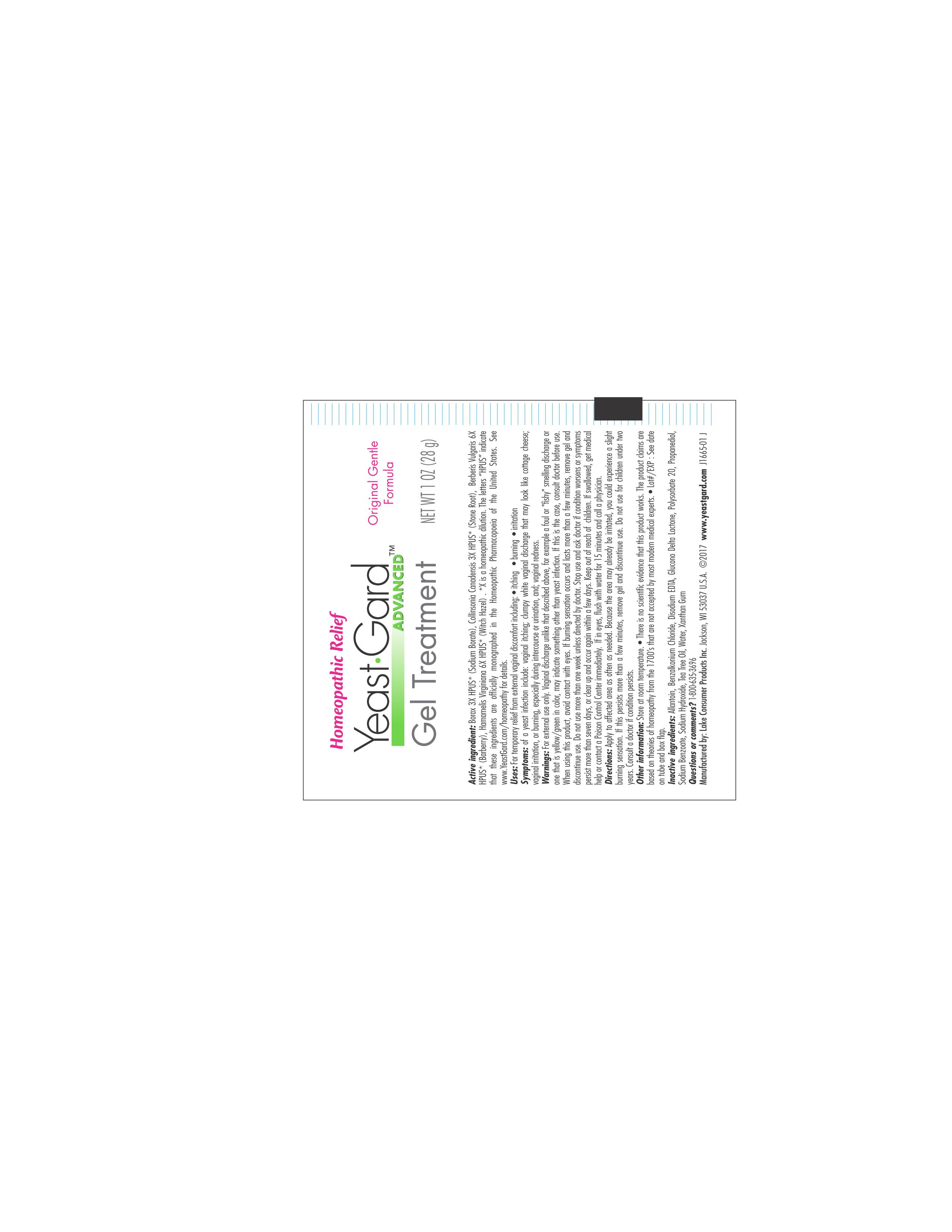 DRUG LABEL: Yeast Gard Homeopathic Gel
NDC: 68093-7247 | Form: GEL
Manufacturer: Wisconsin Pharmacal Company
Category: homeopathic | Type: HUMAN OTC DRUG LABEL
Date: 20181206

ACTIVE INGREDIENTS: HAMAMELIS VIRGINIANA ROOT BARK/STEM BARK 6 [hp_X]/1 g; COLLINSONIA CANADENSIS ROOT 3 [hp_X]/1 g; SODIUM BORATE 3 [hp_X]/1 g; BERBERIS VULGARIS ROOT BARK 6 [hp_X]/1 g
INACTIVE INGREDIENTS: PROPANEDIOL; XANTHAN GUM; SODIUM HYDROXIDE; SODIUM BENZOATE; GLUCONOLACTONE; EDETATE DISODIUM; ALLANTOIN, (+)-; BENZALKONIUM CHLORIDE; WATER; POLYSORBATE 20; TEA TREE OIL

Active Ingredients

Borax 3X HPUS

Collinsonia Canadensis 3X HPUS

Berberis Vulgaris 6X HPUS

Hamamelis Virginiana 6X HPUS

PURPOSE

Purpose Temporary relief from external vagianl discomfort including itching, burning, and irritation

INDICATIONS AND USAGE

Uses For temporary relief of symptoms associate with vaginal yeast infection, including:itching, burning, and irritation.

Warnings

For external vaginal use only. Use only as directed.

Keep out of reach of children. If swallowed, get medial help or contact a Poison Control Center right away. If in eyes, flush with water for 15 minutes and call a physician.

Stop use and ask doctor if

- Symptoms worsen, last more than 7 days, or clear up and occur again within a few days.
- You get a rash or hives, abdominal pain, fever, chills, nausea, vomiting, or foul-smelling vaginal discharge.

Do not use if

- you have never had a vaginal yeast infection diagnosed by a doctor.

When using this product

- Wash hands thoroughly with soap and water before and after use
- Avoid contact with eyes
- If burning sensation occurs and lasts more than a few minutes, remove gel and discontinue use
- Do not use more than one week unless directed by a doctor
- If yoyu do not get complete relief ask a doctor before using another product.

Ask a doctor before use if you have

- Vaginal itching and discomfort for the first time
- Lower abdominal, back or shoulder pain, fever, chills, nausea, vomiting, or foul-smelling vaginal discharge. You may have a serious condition.
- Vaginal yeast infections often (such as once a month or 3 in 6 months). You could be pregnant or have a serious underlying medical cause for you symptoms, including diabetes or a weakened immune system.
- Been exposed to the human immunodeficiency virus (HIV) that causes AIDS
- You have an STD (sexually transmitted disease) or PID (Pelvic inflammatory disease)
- You have frequent and painful urination

PREGNANCY OR BREAST FEEDING

If pregnant or breast-feeding, ask a health professional before use.

Directions

- Apply to affected area as often as needed. Because the area is irritated, you could experience a slight burning sensation. If this persists more than a few minutes, remove gel and discontinue use.
- Wash hand thoroughly with soap an dwater before and after use.
- Do not use for children under two years. Consult a doctor if condition persists.

Inactive Ingredients

Allantoin, Benzalkonium Chloride 50%, Disodium EDTA, Glucono Delta Lactone, Polysorbate 20, Propanediol, Sodium Benzoate, Sodium Hydroxide, Tea Tree Oil, Water, Xanthan Gum

Other Information

- Do not use if safety seal under cap is missing or broken
- Store at room temperature
- Lot number and expiration date: see date on tube and box flap.
- Retain carton for complete Drug Facts Warnings
- There is no scientific evidence that this product works. Ther product claims are based on theories of homeopathy from the 1700's that are not accepted by most modern medical experts.

Questions or comments? 1-800-635-3696